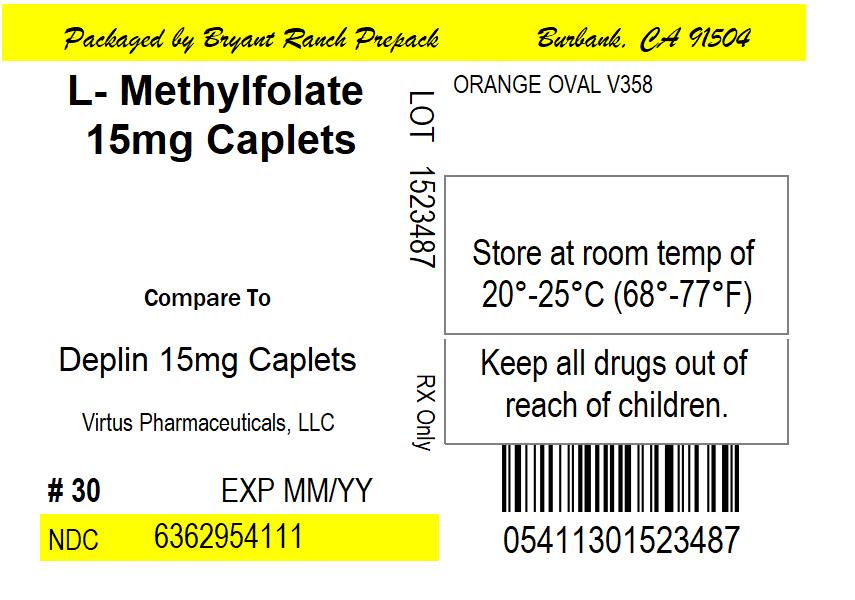 DRUG LABEL: L-Methylfolate Calcium
NDC: 63629-5411 | Form: TABLET, COATED
Manufacturer: Bryant Ranch Prepack
Category: other | Type: MEDICAL FOOD
Date: 20220209

ACTIVE INGREDIENTS: LEVOMEFOLATE CALCIUM 15 mg/1 1
INACTIVE INGREDIENTS: DIBASIC CALCIUM PHOSPHATE DIHYDRATE; POLYVINYL ALCOHOL, UNSPECIFIED; POLYETHYLENE GLYCOL 3350; TALC; TITANIUM DIOXIDE; FD&C YELLOW NO. 6; FD&C YELLOW NO. 5; FD&C RED NO. 40; FD&C BLUE NO. 2; MAGNESIUM STEARATE; CARNAUBA WAX

L-METHYLFOLATE CALCIUM 7.5mg Tablets
L-METHYLFOLATE CALCIUM 15mg Tablets

DESCRIPTION

L-METHYLFOLATE CALCIUM Tablets is a medical food dispensed by prescription for the clinical dietary management of the metabolic imbalances associated with depression and schizophrenia. Use under medical supervision.

Each L-METHYLFOLATE CALCIUM 7.5mg tablet contains 7.5 mg of L-METHYLFOLATE CALCIUM

Each L-METHYLFOLATE CALCIUM 15mg tablet contains 15mg of L-METHYLFOLATE CALCIUM .

L-METHYLFOLATE CALCIUM Tablets 7.5mg Dietary Ingredients

Dibasic Calcium Phosphate Dihydrate, Silicified Microcrystalline Cellulose 90, Silicified Microcrystalline Cellulose HD 90, Opadry II Blue 85F90748 (Polyvinyl Alcohol, Titanium Dioxide [color], PEG 3350, Talc and FD&C Blue #2[color]), L-METHYLFOLATE CALCIUM, Magnesium Stearate (Vegetable Source), and Carnauba Wax.

L-METHYLFOLATE CALCIUM 7.5mg tablets do not contain sugar, lactose, yeast or gluten.

L-METHYLFOLATE CALCIUM 15mg Tablets Dietary Ingredients

Dibasic Calcium Phosphate Dihydrate, Silicified Microcrystalline Cellulose 90, Opadry II Orange 85F43102, (Polyvinyl Alcohol, PEG 3350, Talc, Titanium Dioxide [color], FD&C Yellow #6[color], FD&C Yellow #5[color], FD&C Red #40[color] and FD&C Blue #2[color]), L-METHYLFOLATE CALCIUM, Magnesium Stearate (Vegetable Source), and Carnauba Wax.

L-METHYLFOLATE CALCIUM 15mg tablets do not contain sugar, lactose, yeast or gluten.

Medical foods are intended for a patient who has a limited or impaired capacity to ingest, digest, absorb, or metabolize ordinary foodstuffs or certain nutrients, or who has other special medically determined nutrient requirements, the dietary management of which cannot be achieved by the modification of the normal diet alone.^1 This product is not an Orange Book product.

L-METHYLFOLATE CALCIUM Tablets is a medical food dispensed by prescription.

CLINICAL PHARMACOLOGY

L-METHYLFOLATE CALCIUM Tablets is a medical food, which consists of a proprietary biologically active folate, derived from food sources.

INDICATIONS AND USAGE

ADJUNCTIVE USE IN MAJOR DEPRESSIVE DISORDER L-METHYLFOLATE CALCIUM Tablets is indicated for the distinct nutritional requirements of individuals who have suboptimal L-METHYLFOLATE CALCIUM Tablets levels in the cerebrospinal fluid, plasma, and/or red blood cells and have major depressive disorder (MDD) with particular emphasis as adjunctive support for individuals who are on an antidepressant.^2-5

ADJUNCTIVE USE IN SCHIZOPHRENIA L-METHYLFOLATE CALCIUM Tablets is indicated for the distinct nutritional requirements of individuals who have or are at risk for hyperhomocysteinemia and have schizophrenia who present with negative symptoms and/or cognitive impairment, with particular emphasis as an adjunctive support for individuals who have stabilized on antipsychotics.^2

L-METHYLFOLATE CALCIUM Tablets is indicated regardless of MTHFR C677T polymorphism genotype.^6

CONTRAINDICATIONS

L-METHYLFOLATE CALCIUM Tablets is contraindicated in patients with known hypersensitivity to any of the components contained in this product.

PRECAUTIONS

General

Folic acid, when administered in daily doses above 0.1mg, may obscure the detection of B12 deficiency (specifically, the administration of folic acid may reverse the hematological manifestations of B12 deficiency, including pernicious anemia, while not addressing the neurological manifestations). L-METHYLFOLATE CALCIUM Tablets may be less likely than folic acid to mask vitamin B12 deficiency.^7,8 Folate therapy alone is inadequate for the treatment of a B12 deficiency.

A major depressive episode may be the initial presentation of bipolar disorder. It is generally believed, (although not established in controlled trials) that treating such an episode with an antidepressant alone may increase the likelihood of a precipitation of a mixed/manic episode in patients at risk for bipolar disorder. L-METHYLFOLATE CALCIUM Tablets is not an antidepressant; however, 5-MTHF has been shown to enhance antidepressant effects of known antidepressants.^2 Caution is recommended in patients with a history of bipolar illness. Patients with depressive symptoms should be adequately screened to determine if they are at risk for bipolar disorder since mood elevation in this population is possible.

Patient Information

L-METHYLFOLATE CALCIUM Tablets is a medical food^1 for use under medical supervision and direction.

L-METHYLFOLATE CALCIUM Tablets is a medical food dispensed by prescription.

Interaction with Drugs

Before using this product, tell your doctor or pharmacist of all the products you use. Keep a list of all your medications with you, and share the list with your doctor and pharmacist. No decrease in effectiveness of drugs has been reported with the use of L-METHYLFOLATE CALCIUM Tablets.

L-METHYLFOLATE CALCIUM Tablets contains folate, which may have interactions the following:

- Antiepileptic drugs (AED): The AED class including, but not limited to, phenytoin, carbamazepine, primidone, valproic acid, phenobarbital and lamotrigine have been shown to impair folate absorption and increase the metabolism of circulating folate. Additionally, concurrent use of folic acid has been associated with enhanced phenytoin metabolism, lowering the level of this AED in the blood and allowing breakthrough seizures to occur.^9,10,12,15
- Capecitabine: Folinic acid (5-formyltetrahydrofolate) may increase the toxicity of Capecitabine.^11
- Dihydrofolate Reductase Inhibitors (DHFRI): DHFIs block the conversion of folic acid to its active forms, and lower plasma and red blood cell folate levels. DHFIs include aminopterin, methotrexate, pyrimethamine, triamterene, and trimethoprim.^12
- Fluoxetine: Fluoxetine exerts a noncompetitive inhibition of the 5-methyltetrahydrofolate active transport in the intestine.^13
- Isotretinoin: Reduced folate levels have occurred in some patients taking isotretinoin,^14
- Nonsteroidal Anti-inflammatory Drugs (NSAIDs): NSAIDs have been shown to inhibit some folate dependent enzymes in laboratory experiments. NSAIDs include ibuprofen, naproxen, indomethacin and sulindac.^12
- Oral Contraceptives: Serum folate levels may be depressed by oral contraceptive therapy. ^12
- Methylprednisolone: Reduced serum folate levels have been noted after treatment with methylpredinisolone. ^12
- Pancreatic Enzymes: Reduced folate levels have occurred in some patients taking pancreatic extracts. ^12
- Pentamidine: Reduced folate levels have been seen with prolonged intravenous pentamidine. ^12
- Metformin treatment in patients with type 2 diabetes decreases serum folate.^16,17
- Warfarin can produce significant impairment in folate status after a 6-month therapy.^18

ADVERSE REACTIONS

Allergic reactions have been reported following the use of oral L-METHYLFOLATE CALCIUM Tablets.

DOSAGE AND ADMINISTRATION

The usual adult dose is 7.5mg to 15mg given daily with or without food or as directed under medical supervision.

HOW SUPPLIED

NDC: 63629-5411-1: 30 Tablets in a BOTTLE

PATENTS

Some or all of the following patents may apply: U.S. Patent No. 6,011,040 U.S. Patent No. 6,441,168B1 and other pending patent applications

REFERENCES

1. United States Food and Drug Administration Title 21 Code of Federal Regulations 101.9(j) (8).
2. Godfrey PSA et al. The Lancet. 1990;336:392-5.
3. Passeri M et al. Aging Clin Exp Res. 1993; 5(1):63-71.
4. Guaraldi GP et al. 1993;5(2):101-5.
5. Di Palma C et al. Is Curr Ther Res. 1994; 55 (5): 559-68.
6. Willems FF et al. Br J Pharmacol.2004;141 (5):825-30.
7. Akoglu B et al. Euro J Clin Nutrition. 2007; 1–6.
8. Scott JM and Weir DG. The Lancet. 1981; 2: 337-40.
9. Hernandez-Diaz. N Engl J Med. 2000; 343: 1608-14.
10. Morrell M. Curr. 2002; 2(2):31–34.
11. Capecitabine Package Insert; Roche Laboratories, 2000
12. Natural Standard Research Collaboration (NIH). Folate (folic acid) Monograph 2009
13. .Amiburu A, et al. J. Physiol. Biochem., 57 (2), 71-80, 2001
14. Chanson A, et al. JEADV 2008, 22:94-100
15. Tatum IV W et al. Arch Intern Med. 2004; 164: 137-45.
16. Wulffele MG, et al. Journal of Internal Medicine 2003; 254: 455-463.
17. Desouza C, et al. Drugs 2002; 62(4): 605-16.
18. Sobczyriska-Malefora A et al. Blood Coagul Fibrinolysis 2009 Jun; 20(4):297-302

Manufactured for:
Virtus Pharmaceuticals, LLC
Tampa, FL 33619

PC0294-00
Revised 11/14

PACKAGE LABEL

L- Methylfolate 15mg Caplets